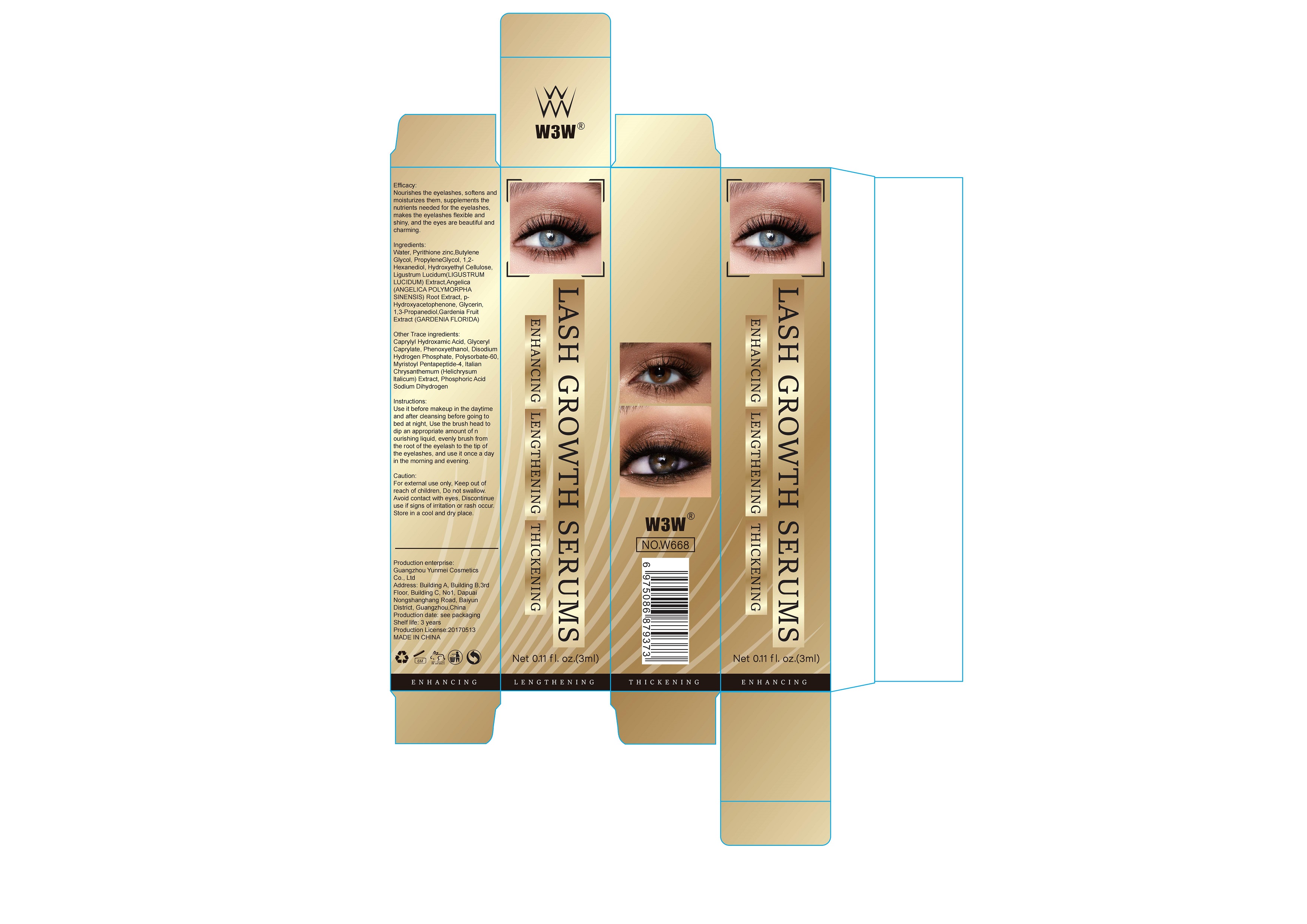 DRUG LABEL: BROW GROWTH SERUMS
NDC: 84718-004 | Form: SOLUTION
Manufacturer: Shenzhen Chuangwei Electronic Technology Co., Ltd.
Category: otc | Type: HUMAN OTC DRUG LABEL
Date: 20241111

ACTIVE INGREDIENTS: PYRITHIONE ZINC 0.2 g/100 mL
INACTIVE INGREDIENTS: WATER; BUTYLENE GLYCOL; GLYCERIN; 1,2-HEXANEDIOL; MYRISTOYL PENTAPEPTIDE-4; PROPYLENE GLYCOL; CAPRYLHYDROXAMIC ACID; GLYCERYL CAPRYLATE; HELICHRYSUM ITALICUM FLOWER OIL; PHENOXYPROPANEDIOL; HYDROXYETHYLCELLULOSE; SODIUM PHOSPHATE, DIBASIC, ANHYDROUS; SODIUM PHOSPHATE, MONOBASIC, ANHYDROUS; PEG-60 SORBITAN STEARATE; GARDENIA JASMINOIDES FRUIT; PROPANEDIOL; LIGUSTRUM LUCIDUM WHOLE; ANGELICA SINENSIS ROOT; HYDROXYACETOPHENONE

Ingredient

Water, Pyrithione zinc,ButyleneGlycol, PropyleneGlycol, 1,2-Hexanediol, Hydroxyethyl CelluloseLigustrum Lucidum(LIGUSTRUMLUCIDUM) Extract,Angelica(ANGELICA POLYMORPHASINENSIS) Root Extract, pHydroxyacetophenone, Glycerin.1,3-Propanediol,Gardenia FruitExtract (GARDENIA FLORIDA)
Other Trace ingredients:Caprylyl Hydroxamic Acid, GlycerylCaprylate, Phenoxyethanol, DisodiumHydrogen Phosphate, Polysorbate-60Myristoyl Pentapeptide-4, ltalianChrysanthemum (Helichrysumltalicum)Extract, Phosphoric AcidSodium Dihydrogen

Caution

For external use only, Keep out ofreach of children, Do not swallow.Avoid contact with eyes, Discontinueuse if signs of irritation or rash occur.Store in a cool and dry place.

INACTIVE INGREDIENT

none

DOSAGE AND ADMINISTRATION

none

instruction

Use it before makeup in the daytimeand after cleansing before going tobed at night, Use the brush head todip an appropriate amount of nourishing liquid, evenly brush fromthe root of the eyelash to the tip ofthe eyelashes, and use it once a dayin the morning and evening

KEEP OUT OF REACH OF CHILDREN

none